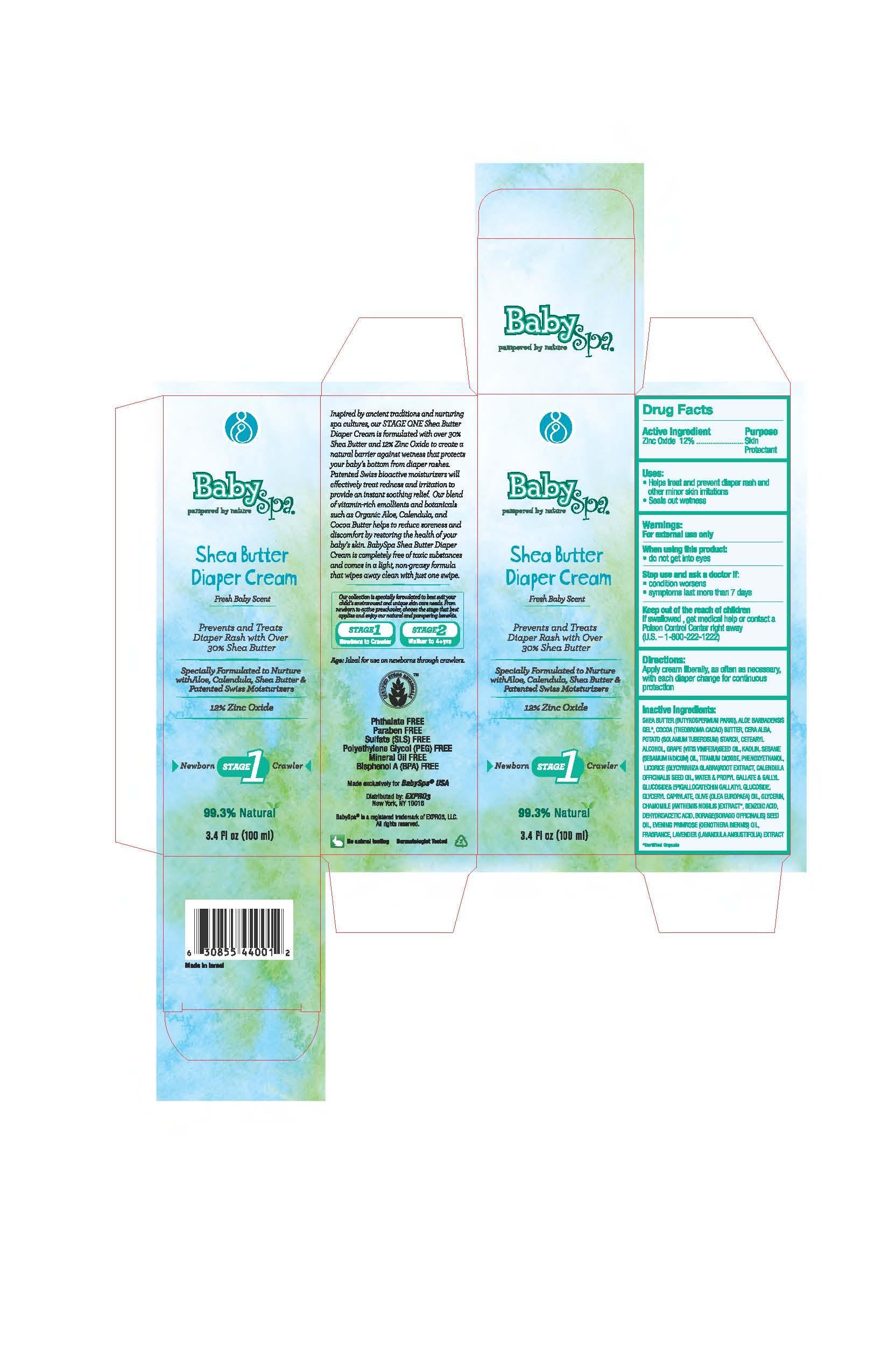 DRUG LABEL: BabySpa
NDC: 42957-001 | Form: CREAM
Manufacturer: EXPRO3 LLC
Category: otc | Type: HUMAN OTC DRUG LABEL
Date: 20120718

ACTIVE INGREDIENTS: Zinc Oxide 120 mg/1 mL
INACTIVE INGREDIENTS: SHEA BUTTER; ALOE VERA FLOWER; COCOA BUTTER; YELLOW WAX; STARCH, POTATO; CETOSTEARYL ALCOHOL; GRAPE SEED OIL; KAOLIN; SESAME OIL; TITANIUM DIOXIDE; PHENOXYETHANOL; GLYCYRRHIZA GLABRA; CALENDULA OFFICINALIS SEED OIL; WATER; PROPYL GALLATE; LAURYL GLUCOSIDE; EPIGALLOCATECHIN GALLATE; GLYCERYL CAPRYLATE; OLIVE OIL; GLYCERIN; CHAMAEMELUM NOBILE FLOWER; BENZOIC ACID; DEHYDROACETIC ACID; BORAGE OIL; OENOTHERA BIENNIS; LAVANDULA ANGUSTIFOLIA FLOWER

Drug Facts
Active Ingredients Purpose
Zinc Oxide 12%......................Skin Protectant

Uses:
* Helps treat and prevent diaper rash and other minor skin irritations
* Seals out wetness

Keep out of reach of children
If swallowed, get medical help or contact a Poison Control Center right away
(U.S. -- 1-800-222-1222)

Directions:
Apply cream liberally, as often as necessary, with each diaper change for continuous protection

Warnings:
For external use only

Stop use and ask a doctor if:
* condition worsens
* symptoms last more than 7 days

INACTIVE INGREDIENT

shea butter (butyrospermum parkii), aloe barbadensis gel, cocoa (theobroma cacao) butter, beeswax, potato (solanium tuberosum) starch, cetearyl alcohol, grape (vitis vinifera) seed oil, kaolin, sesame (sesamum indicum) oil, titanium dioxide, phenoxyethanol, licorice (glycyrrhiza glabra) root extract, calendula officinalis seed oil, Unisooth EG-28 (water propyl gallate gallyl glucoside epigallocatechin gallatyl glucoside), glyceryl caprylate, olive (olea europaea) oil*, glycerin, chamomile (anthemis nobilis) extract, benzoic acid, dehydroacetic acid, borage (borago officinalis) seed oil, evening primrose (oenothera biennis) oil, fragrance, lavender (lavandula angustifolia) extract.